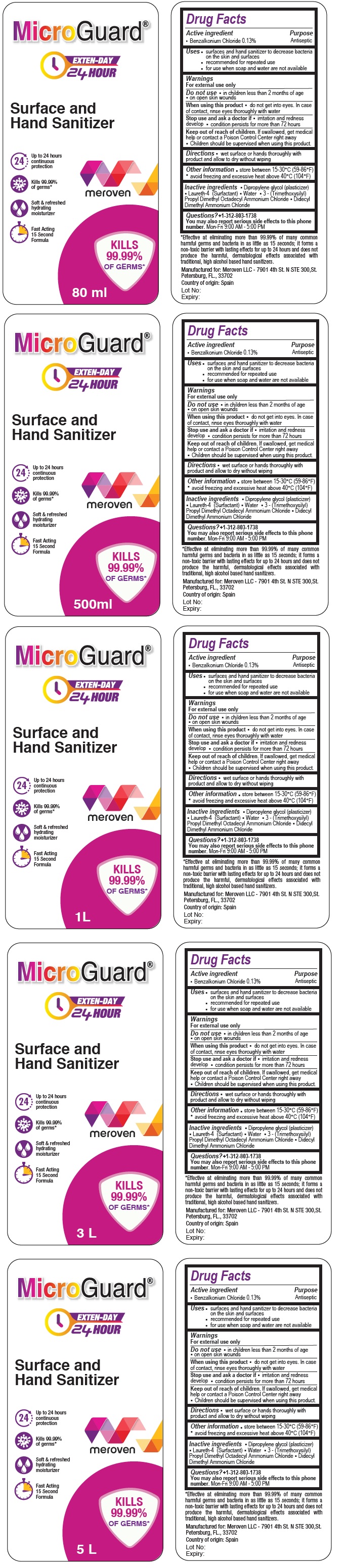 DRUG LABEL: Micro Guard 24 HOUR Surface and Hand Sanitizer
NDC: 74653-105 | Form: LIQUID
Manufacturer: Meroven Llc
Category: otc | Type: HUMAN OTC DRUG LABEL
Date: 20200707

ACTIVE INGREDIENTS: BENZALKONIUM CHLORIDE 1.3 mg/1 mL
INACTIVE INGREDIENTS: DIPROPYLENE GLYCOL; LAURETH-4; WATER; DIMETHYLOCTADECYL(3-(TRIMETHOXYSILYL)PROPYL)AMMONIUM CHLORIDE; DIDECYLDIMONIUM CHLORIDE

MicroGuard® 24 HOUR Surface and Hand Sanitizer

Active ingredient

Benzalkonium Chloride 0.13%

Purpose

Antiseptic

Uses

- surfaces and hand sanitizer to decrease bacteria on the skin and surfaces
- recommended for repeated use
- for use when soap and water are not available

Warnings
For external use only

Do not use •in children less than 2 months of age • on open skin wounds

When using this product • do not get into eyes. In case of contact, rinse eyes thoroughly with water

Stop use and ask a doctor if •irritation and redness develop condition persists for more than 72 hours

Keep out of reach of children. If swallowed, get medical help or contact a Poison Control Center right away Children should be supervised when using this product.

DOSAGE AND ADMINISTRATION

Directions •wet surface or hands thoroughly with product and allow to dry without wiping

Other information• store between 15-30°C (59-86°F) • avoid freezing and excessive heat above 40°C (104°F)

INACTIVE INGREDIENT

Inactive ingredients • Dipropylene glycol (plasticizer) • Laureth-4 (Surfactant) • Water • 3 - (Trimethoxysilyl) Propyl Dimethyl Octadecyl Ammonium Chloride • Didecyl Dimethyl Ammonium Chloride

Questions? +1-312-803-1738
You may also report serious side effects to this phone number. Mon-Fri 9:00 AM - 5:00 PM

EXTEN-DAY 24 HOUR

24 Up to 24 hours continuous protection

Kills 99.99% of germs*

Soft & refreshed hydrating moisturizer

Fast Acting 15 Second Formula

*Effective at eliminating more than 99.99% of many common harmful germs and bacteria in as little as 15 seconds; it forms a non-toxic barrier with lasting effects for up to 24 hours and does not produce the harmful, dermatological effects associated with traditional, high alcohol based hand sanitizers.

Manufactured for: Meroven LLC - 7901 4th St. N STE 300,St.Petersburg, FL., 33702

Country of origin: Spain